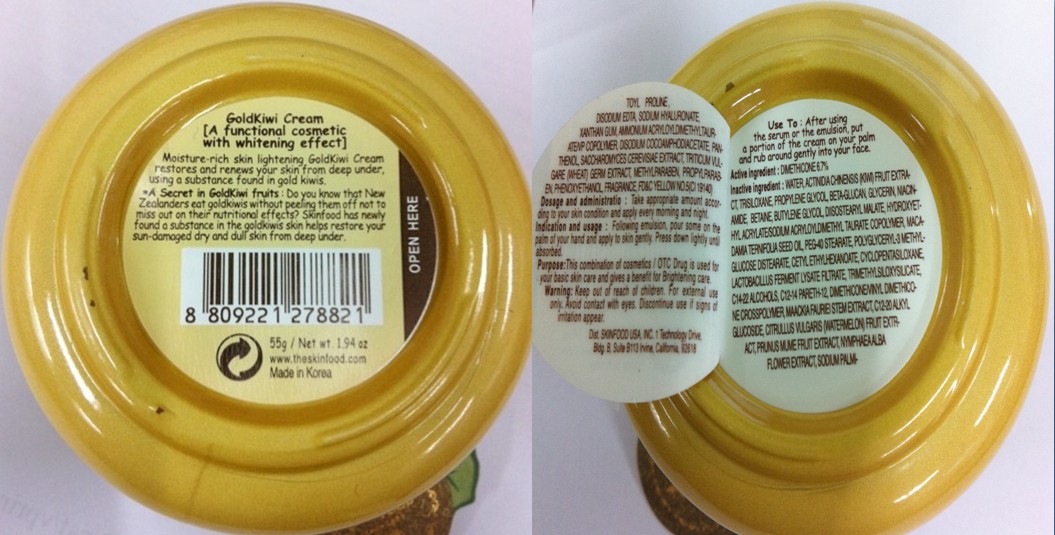 DRUG LABEL: GOLDKIWI
NDC: 76214-002 | Form: CREAM
Manufacturer: SKINFOOD CO., LTD.
Category: otc | Type: HUMAN OTC DRUG LABEL
Date: 20110727

ACTIVE INGREDIENTS: DIMETHICONE 3.69 g/55 g
INACTIVE INGREDIENTS: WATER; ACTINIDIA CHINENSIS SEED; TRISILOXANE; PROPYLENE GLYCOL; GLYCERIN; NIACINAMIDE; BETAINE; BUTYLENE GLYCOL; MACADAMIA OIL; PEG-40 STEARATE; CETYL ETHYLHEXANOATE; CYCLOMETHICONE 5; C14-22 ALCOHOLS; MAACKIA FLORIBUNDA STEM; METHYLPARABEN; PHENOXYETHANOL; C12-20 ALKYL GLUCOSIDE; PRUNUS MUME FRUIT; PROPYLPARABEN; NYMPHAEA ALBA FLOWER; SODIUM PALMITOYL PROLINE; EDETATE DISODIUM; XANTHAN GUM; DISODIUM COCOAMPHODIACETATE; PANTHENOL; SACCHAROMYCES CEREVISIAE; WHEAT GERM

Drug Facts

Active ingredient: DIMETHICONE 6.7%

Inactive ingredients:

WATER, ACTINIDIA CHINENSIS (KIWI) FRUIT EXTRACT, TRISILOXANE, PROPYLENE GLYCOL, BETA-GLUCAN, GLYCERIN, NIACINAMIDE, BETAINE, BUTYLENE GLYCOL, DIISOSTEARYL MALATE, HYDROXYETHYL ACRYLATE/SODIUM ACRYLOYLDIMETHYL TAURATE COPOLYMER, MACADAMIA TERNIFOLIA SEED OIL, PEG-40 STEARATE, POLYGLYCERYL-3 METHYLGLUCOSE DISTEARATE, CETYL ETHYLHEXANOATE, CYCLOPENTASILOXANE, LACTOBACILLUS FERMENT LYSATE FILTRATE, TRIMETHYLSILOXYSILICATE, C14-22 ALCOHOLS, C12-14 PARETH-12, DIMETHICONE/VINYL DIMETHICONE CROSSPOLYMER, MAACKIA FAURIEI STEM EXTRACT, C12-20 ALKYL GLUCOSIDE, CITRULLUS VULGARIS (WATERMELON) FRUIT EXTRACT, PRUNUS MUME FRUIT EXTRACT, NYMPHAEA ALBA FLOWER EXTRACT, SODIUM PALMITOYL PROLINE, DISODIUM EDTA, SODIUM HYALURONATE, XANTHAN GUM, AMMONIUM ACRYLOYLDIMETHYLTAURATE/VP COPOLYMER, DISODIUM COCOAMPHODIACETATE, PANTHENOL, SACCHAROMYCES CEREVISIAE EXTRACT, TRITICUM VULGARE (WHEAT) GERM EXTRACT, METHYLPARABEN, PROPYLPARABEN, PHENOXYETHANOL, FRAGRANCE

Purpose:

This combination of cosmetics is used for your basic skin care and gives a benefit for Brightening care.

Warnings:

For external use only. Avoid contact with eyes. Discontinue use if signs of irritation appear.

Keep out of reach of children:

Keep out of reach of children.

Indication and usage:

Following emulsion, pour some on the palm of your hand and apply to skin gently. Press down lightly until absorbed.

Dosage and administration:

Take appropriate amount according to your skin condition and apply every morning and night.